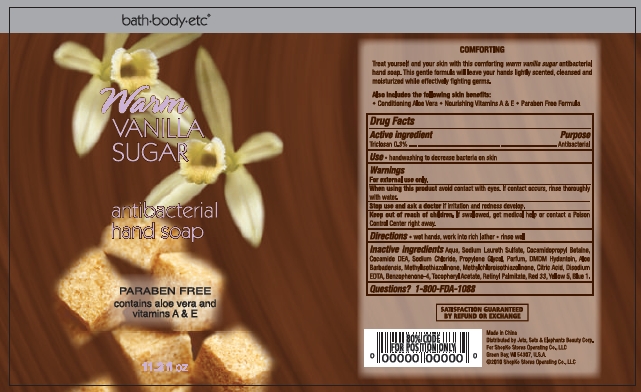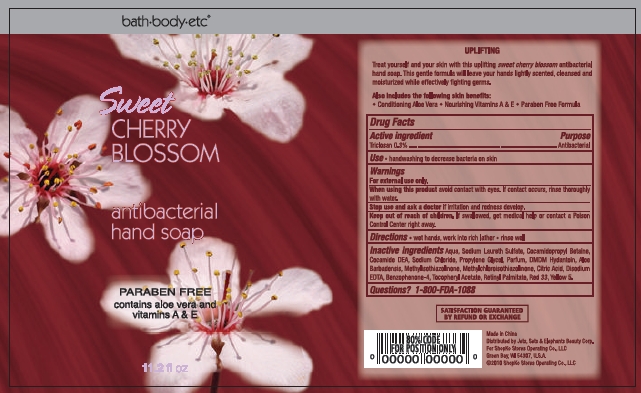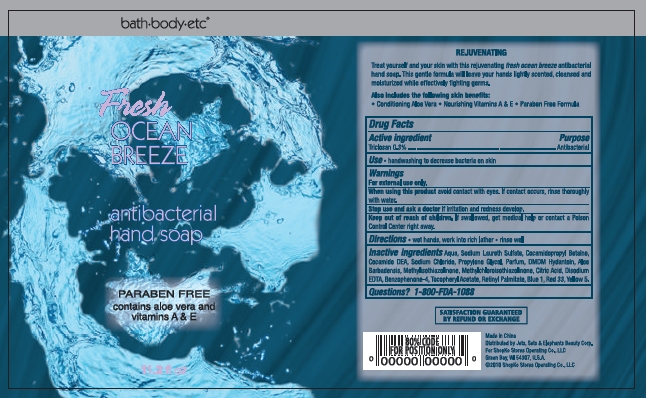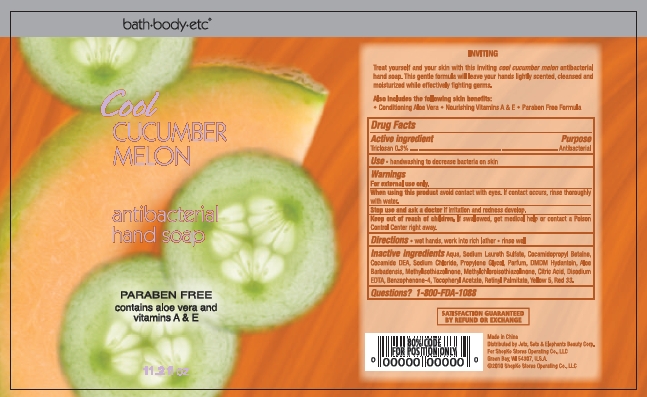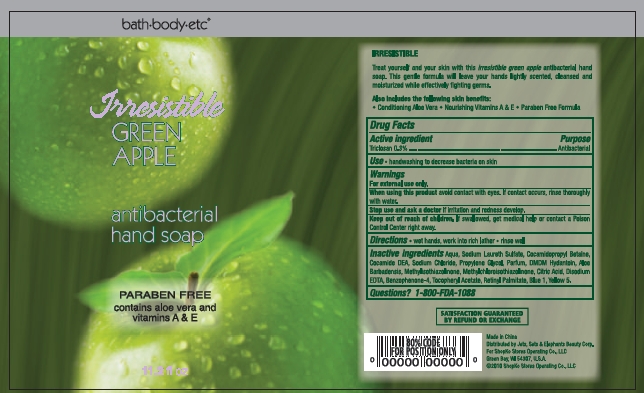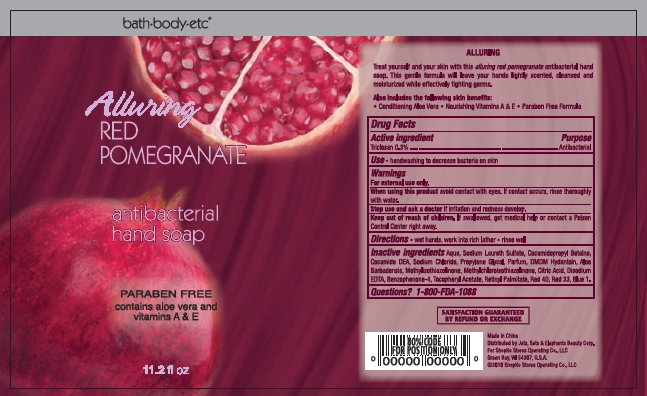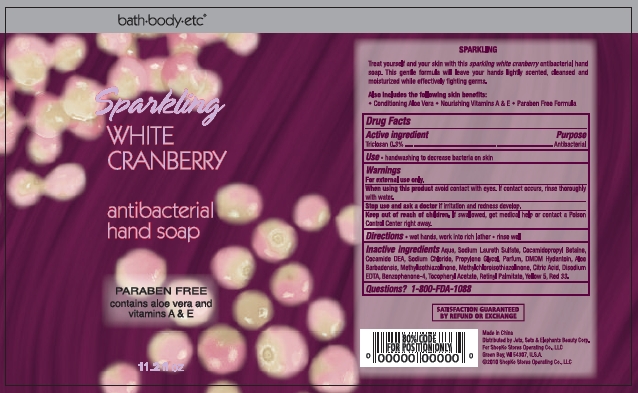 DRUG LABEL: Antibacterial Hand Soap
NDC: 50988-210 | Form: SOLUTION
Manufacturer: Jets, Sets, & Elephants Beauty Corp.
Category: otc | Type: HUMAN OTC DRUG LABEL
Date: 20100802

ACTIVE INGREDIENTS: TRICLOSAN 0.994 mL/331.22 mL
INACTIVE INGREDIENTS: WATER; SODIUM LAURETH SULFATE; COCAMIDOPROPYL BETAINE; COCO DIETHANOLAMIDE; SODIUM CHLORIDE; PROPYLENE GLYCOL; DMDM HYDANTOIN; ALOE VERA LEAF; METHYLISOTHIAZOLINONE; METHYLCHLOROISOTHIAZOLINONE; CITRIC ACID MONOHYDRATE; EDETATE CALCIUM DISODIUM ANHYDROUS; SULISOBENZONE; .ALPHA.-TOCOPHEROL ACETATE, D-; VITAMIN A PALMITATE; D&C RED NO. 33; FD&C BLUE NO. 1; FD&C YELLOW NO. 5

bath+body+etc® antibacterial hand soap - Warm Vanilla Sugar, Sweet Cherry Blossom, Fresh Ocean Breeze, Cool Cucumber Melon, Irresistible Green Apple, Alluring Red Pomegranate, Sparkling White Cranberry

Active ingredient

Triclosan 0.3%

Purpose

Antibacterial

Uses

- handwashing to decrease bacteria on skin

Warnings

For external use only.

When using this product avoid contact with eyes. If contact occurs, rinse thoroughly with water.

Stop use and ask a doctor if irritation and redness develop.

Keep out of reach of children. If swallowed, get medical help or contact a Poison Control Center right away.

Directions

- wet hands, work into rich lather
- rinse well

Inactive Ingredients

Warm Vanilla Sugar

Aqua, Sodium Laureth Sulfate, Cocamidopropyl Betaine, Cocamide DEA, Sodium Chloride, Propylene Glycol, Parfum, DMDM Hydantoin, Aloe Barbadensis, Methylisothiazolinone, Methylchloroisothiazolinone, Citric Acid, Disodium EDTA, Benzophenone-4, Tocopheryl Acetate, Retinyl Palmitate, Red 33, Blue 1, Yellow 5

Sweet Cherry Blossom

Aqua, Sodium Laureth Sulfate, Cocamidopropyl Betaine, Cocamide DEA, Sodium Chloride, Propylene Glycol, Parfum, DMDM Hydantoin, Aloe Barbadensis, Methylisothiazolinone, Methylchloroisothiazolinone, Citric Acid, Disodium EDTA, Benzophenone-4, Tocopheryl Acetate, Retinyl Palmitate, Red 33, Yellow 5

Fresh Ocean Breeze

Aqua, Sodium Laureth Sulfate, Cocamidopropyl Betaine, Cocamide DEA, Sodium Chloride, Propylene Glycol, Parfum, DMDM Hydantoin, Aloe Barbadensis, Methylisothiazolinone, Methylchloroisothiazolinone, Citric Acid, Disodium EDTA, Benzophenone-4, Tocopheryl Acetate, Retinyl Palmitate, Red 33, Blue 1, Yellow 5

Cool Cucumber Melon

Aqua, Sodium Laureth Sulfate, Cocamidopropyl Betaine, Cocamide DEA, Sodium Chloride, Propylene Glycol, Parfum, DMDM Hydantoin, Aloe Barbadensis, Methylisothiazolinone, Methylchloroisothiazolinone, Citric Acid, Disodium EDTA, Benzophenone-4, Tocopheryl Acetate, Retinyl Palmitate, Red 33, Yellow 5

Irresistible Green Apple

Aqua, Sodium Laureth Sulfate, Cocamidopropyl Betaine, Cocamide DEA, Sodium Chloride, Propylene Glycol, Parfum, DMDM Hydantoin, Aloe Barbadensis, Methylisothiazolinone, Methylchloroisothiazolinone, Citric Acid, Disodium EDTA, Benzophenone-4, Tocopheryl Acetate, Retinyl Palmitate, Blue 1, Yellow 5

Alluring Red Pomegranate

Aqua, Sodium Laureth Sulfate, Cocamidopropyl Betaine, Cocamide DEA, Sodium Chloride, Propylene Glycol, Parfum, DMDM Hydantoin, Aloe Barbadensis, Methylisothiazolinone, Methylchloroisothiazolinone, Citric Acid, Disodium EDTA, Benzophenone-4, Tocopheryl Acetate, Retinyl Palmitate, Red 40, Red 33, Blue 1

Sparkling White Cranberry

Aqua, Sodium Laureth Sulfate, Cocamidopropyl Betaine, Cocamide DEA, Sodium Chloride, Propylene Glycol, Parfum, DMDM Hydantoin, Aloe Barbadensis, Methylisothiazolinone, Methylchloroisothiazolinone, Citric Acid, Disodium EDTA, Benzophenone-4, Tocopheryl Acetate, Retinyl Palmitate, Red 33, Yellow 5

Questions?

1-800-FDA-1088

SATISFACTION GUARANTEED BY REFUND OR EXCHANGE

Made in China

Distributed by Jets, Sets & Elephants Beauty Corp.

For Shopko Stores Operating Co., LLC

Green Bay, WI 54307, U.S.A.

©2010 Shopko Stores Operating Co., LLC

Package/Label Principal Display Panel - Bottle Label

bath+body+etc®

Warm

VANILLA SUGAR

antibacterial

hand soap

PARABEN FREE

contains aloe vera and

vitamins A & E

11.2 fl oz

Warm Vanilla Sugar Bottle Label

Package/Label Principal Display Panel - Bottle Label

bath+body+etc®

Sweet

CHERRY BLOSSOM

antibacterial

hand soap

PARABEN FREE

contains aloe vera and

vitamins A & E

11.2 fl oz

Sweet Cherry Blossom Bottle Label

Package/Label Principal Display Panel - Bottle Label

bath+body+etc®

Fresh

OCEAN BREEZE

antibacterial

hand soap

PARABEN FREE

contains aloe vera and

vitamins A & E

11.2 fl oz

Fresh Ocean Breeze Bottle Label

Package/Label Principal Display Panel - Bottle Label

bath+body+etc®

Cool

CUCUMBER MELON

antibacterial

hand soap

PARABEN FREE

contains aloe vera and

vitamins A & E

11.2 fl oz

Cool Cucumber Melon Bottle Label

Package/Label Principal Display Panel - Bottle Label

bath+body+etc®

Irresistible

GREEN APPLE

antibacterial

hand soap

PARABEN FREE

contains aloe vera and

vitamins A & E

11.2 fl oz

Irresistible Green Apple Bottle Label

Package/Label Principal Display Panel - Bottle Label

bath+body+etc®

Alluring

RED POMEGRANATE

antibacterial

hand soap

PARABEN FREE

contains aloe vera and

vitamins A & E

11.2 fl oz

Alluring Red Pomegranate Bottle Label

Package/Label Principal Display Panel - Bottle Label

bath+body+etc®

Sparkling

WHITE CRANBERRY

antibacterial

hand soap

PARABEN FREE

contains aloe vera and

vitamins A & E

11.2 fl oz

Sparkling White Cranberry Bottle Label